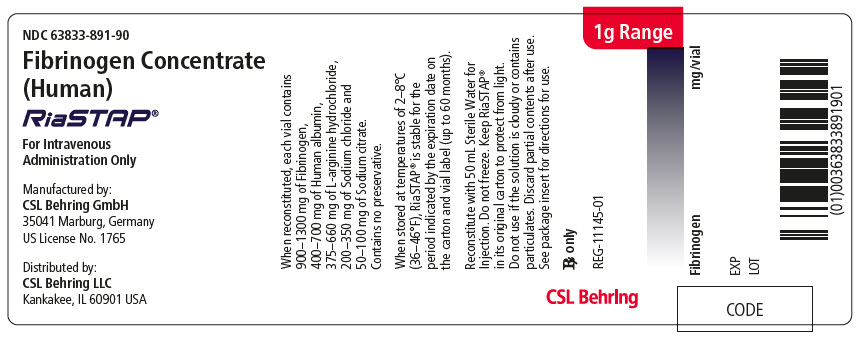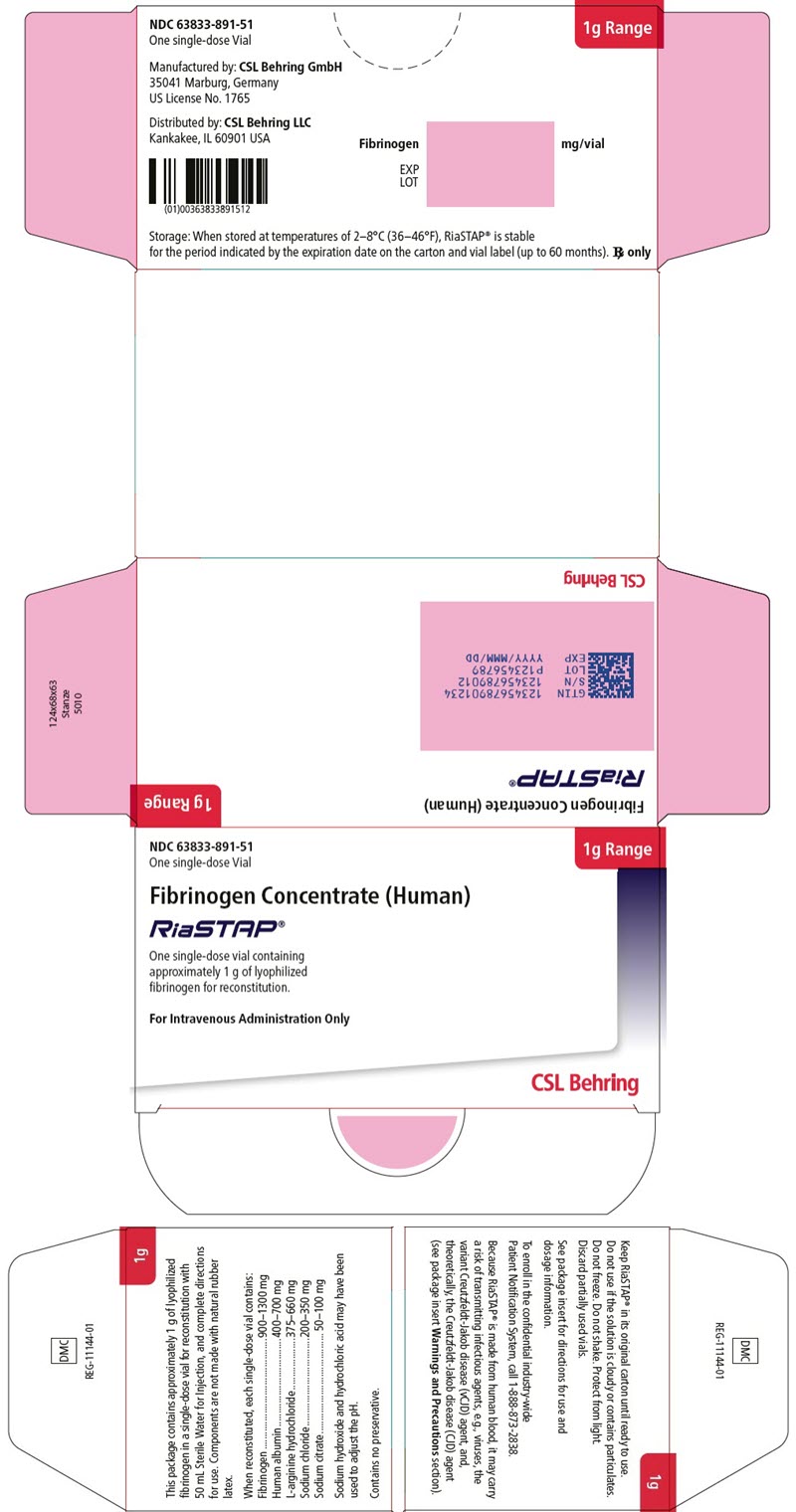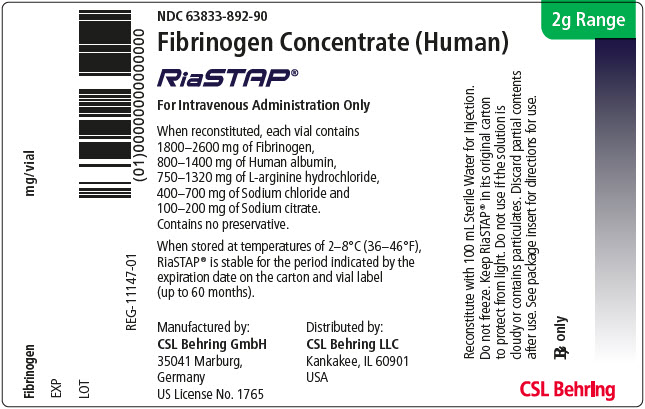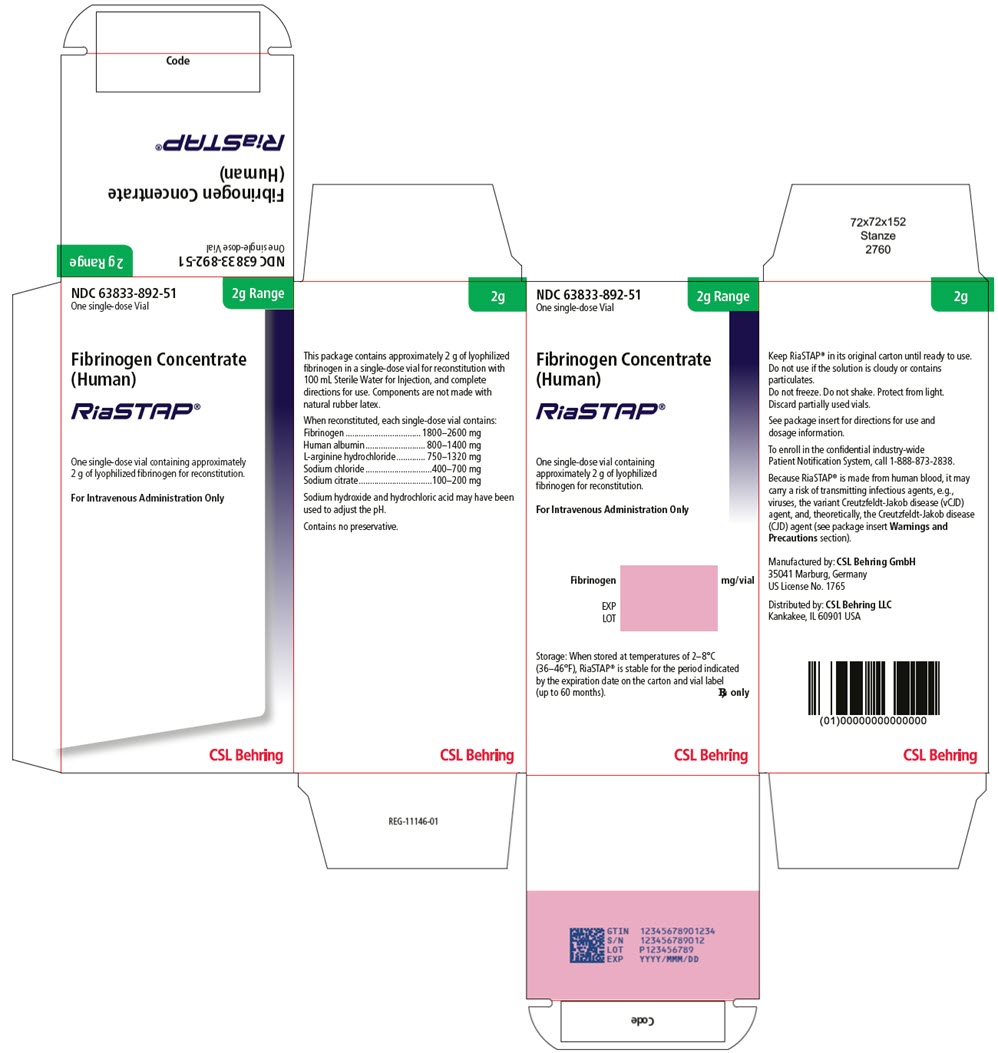 DRUG LABEL: RiaSTAP
NDC: 63833-891 | Form: INJECTION, POWDER, LYOPHILIZED, FOR SOLUTION
Manufacturer: CSL Behring GmbH
Category: other | Type: PLASMA DERIVATIVE
Date: 20251229

ACTIVE INGREDIENTS: FIBRINOGEN HUMAN 1300 mg/50 mL
INACTIVE INGREDIENTS: Albumin Human 700 mg/50 mL; arginine hydrochloride 660 mg/50 mL; Sodium chloride 350 mg/50 mL; Sodium citrate, unspecified form 100 mg/50 mL; Water; Sodium hydroxide; hydrochloric acid

HIGHLIGHTS OF PRESCRIBING INFORMATION

These highlights do not include all the information needed to use RIASTAP® safely and effectively. See full prescribing information for RIASTAP.
RIASTAP, Fibrinogen Concentrate (Human)
Lyophilized Powder for Solution for Intravenous Injection
Initial U.S. Approval: 2009

RECENT MAJOR CHANGES

Dosage and Administration, Preparation and Reconstitution (2.2) | 12/2025

1 INDICATIONS AND USAGE

RIASTAP, Fibrinogen Concentrate (Human) is a human blood coagulation factor indicated for the treatment of acute bleeding episodes in pediatric and adult patients with congenital fibrinogen deficiency, including afibrinogenemia and hypofibrinogenemia. (1)

RIASTAP is not indicated for dysfibrinogenemia.

2 DOSAGE AND ADMINISTRATION

For intravenous use only.

- Dose (mg/kg body weight) =
  [Target level (mg/dL) - measured level (mg/dL)]
  1.7 (mg/dL per mg/kg body weight)
- Dose when fibrinogen level is unknown: 70 mg/kg body weight. (2.1)
- Monitoring of patient's fibrinogen level is recommended during treatment. A target fibrinogen level of 100 mg/dL should be maintained until hemostasis is obtained. (2.1)
- Injection rate should not exceed 5 mL per minute. (2.3)

3 DOSAGE FORMS AND STRENGTHS

- RIASTAP is available as a single-dose vial containing approximately 1 or 2 g lyophilized fibrinogen concentrate powder for reconstitution. (3)
- The actual fibrinogen potency for each lot is printed on the vial label and carton. (3)

4 CONTRAINDICATIONS

Known anaphylactic or severe systemic reactions to human plasma-derived products (4)

5 WARNINGS AND PRECAUTIONS

- Monitor patients for early signs of anaphylaxis or hypersensitivity reactions and if necessary, discontinue administration and institute appropriate treatment. (5.1)
- Thrombotic events have been reported in patients receiving RIASTAP. Weigh the benefits of administration versus the risks of thrombosis. (5.2)
- Because RIASTAP is made from human blood, it may carry a risk of transmitting infectious agents, e.g., viruses, the variant Creutzfeldt-Jakob disease (vCJD) agent and, theoretically, the Creutzfeldt-Jakob disease (CJD) agent. (5.3)

6 ADVERSE REACTIONS

- The most serious adverse reactions observed are thrombotic episodes (pulmonary embolism, myocardial infarction, deep vein thrombosis) and anaphylactic reactions. (6)
- The most common adverse reactions observed in clinical studies (frequency >1%) were fever and headache. (6)

To report SUSPECTED ADVERSE REACTIONS, contact CSL Behring at 1-866-915-6958 or FDA at 1-800-FDA-1088 or www.fda.gov/medwatch.

8 USE IN SPECIFIC POPULATIONS

- Pediatric: Shorter half-life and faster clearance than in adults has been observed. (8.4)

FULL PRESCRIBING INFORMATION

1 INDICATIONS AND USAGE

RIASTAP®, Fibrinogen Concentrate (Human) is a human blood coagulation factor indicated for the treatment of acute bleeding episodes in pediatric and adult patients with congenital fibrinogen deficiency, including afibrinogenemia and hypofibrinogenemia.

Limitation of Use

RIASTAP is not indicated for dysfibrinogenemia.

2 DOSAGE AND ADMINISTRATION

For intravenous use only.

2.1 Treatment of Congenital Fibrinogen Deficiency

RIASTAP dosing, duration of dosing and frequency of administration should be individualized based on the extent of bleeding, laboratory values, and the clinical condition of the patient.

RIASTAP dose when baseline fibrinogen level is known.

Dose should be individually calculated for each patient based on the target plasma fibrinogen level based on the type of bleeding, actual measured plasma fibrinogen level and body weight, using the following formula [see Clinical Pharmacology (12.3)]:

[Target level (mg/dL) - measured level (mg/dL)]

1.7 (mg/dL per mg/kg body weight)

RIASTAP dose when baseline fibrinogen level is not known.

If the patient's fibrinogen level is not known, the recommended dose is 70 mg per kg of body weight administered intravenously.

Monitor patient's fibrinogen level during treatment with RIASTAP. Maintain a target fibrinogen level of 100 mg/dL until hemostasis is obtained.

2.2 Preparation and Reconstitution

The procedures below are provided as general guidelines for preparation and reconstitution of RIASTAP.

Use aseptic technique when preparing and reconstituting RIASTAP.

Reconstitute RIASTAP at room temperature as follows:

1. Remove the cap from the product vial to expose the central portion of the rubber stopper.
2. Clean the surface of the rubber stopper with an antiseptic solution and allow it to dry.
3. Using an appropriate transfer device or syringe, transfer 50 mL (for 1 g dose vial) or 100 mL (for 2 g dose vial) of Sterile Water for Injection into the product vial.
4. Gently swirl the product vial to ensure the product is fully dissolved. Do not shake the vial.

After reconstitution, the RIASTAP solution should be colorless and clear to slightly opalescent. Inspect visually for particulate matter and discoloration prior to administration. Do not use if the solution is cloudy or contains particulates. Discard partially used vials.

RIASTAP is stable for 8 hours after reconstitution when stored at 20-25°C; administer within this time period.

Before administration, filter reconstituted RIASTAP solution with a 17-micron filter (not supplied) into an appropriate syringe.

2.3 Administration

Do not mix RIASTAP with other medicinal products or intravenous solutions. Administer through a separate injection site.

Use aseptic technique when administering RIASTAP.

Administer RIASTAP at room temperature by slow intravenous injection at a rate not exceeding 5 mL per minute.

3 DOSAGE FORMS AND STRENGTHS

RIASTAP 1 g dose vial

RIASTAP is available as a single-dose vial containing approximately 1 g lyophilized fibrinogen concentrate powder for reconstitution with 50 mL of Sterile Water for Injection.

RIASTAP 2 g dose vial

RIASTAP is available as a single-dose vial containing approximately 2 g lyophilized fibrinogen concentrate powder for reconstitution with 100 mL of Sterile Water for Injection.

The actual fibrinogen potency for each lot is printed on the vial label and carton.

4 CONTRAINDICATIONS

RIASTAP is contraindicated in patients with known anaphylactic or severe systemic reactions to human plasma-derived products.

5 WARNINGS AND PRECAUTIONS

5.1 Hypersensitivity Reactions

Allergic reactions may occur. If signs or symptoms of anaphylaxis or hypersensitivity reactions (including hives, generalized urticaria, tightness of the chest, wheezing, hypotension) occur, immediately discontinue administration [see Patient Counseling Information (17)]. The treatment required depends on the nature and severity of the reaction.

5.2 Thrombosis

Thrombosis may occur spontaneously in patients with congenital fibrinogen deficiency with or without the use of fibrinogen replacement therapy.^1 Thromboembolic events have been reported in patients treated with RIASTAP. Weigh the benefits of RIASTAP administration versus the risk of thrombosis. Monitor patients receiving RIASTAP for signs and symptoms of thrombosis [see Patient Counseling Information (17)].

5.3 Transmissible Infectious Agents

Because RIASTAP is made from human blood, it may carry a risk of transmitting infectious agents, e.g., viruses, the variant Creutzfeldt-Jakob disease (vCJD) agent and, theoretically, the Creutzfeldt-Jakob disease (CJD) agent. The risk that such products will transmit an infectious agent has been reduced by screening plasma donors for prior exposure to certain viruses, by testing for the presence of certain current virus infections, and by a process demonstrated to inactivate and/or remove certain viruses during manufacturing [see Description (11)]. Despite these measures, such products may still potentially transmit disease. There is also the possibility that unknown infectious agents may be present in such products [see Patient Counseling Information (17)]. All infections thought by a physician possibly to have been transmitted by this product should be reported by the physician or other healthcare provider to CSL Behring Pharmacovigilance at 1-866-915-6958.

6 ADVERSE REACTIONS

The most serious adverse reactions reported in clinical studies or through postmarketing surveillance following RIASTAP treatment are thromboembolic episodes, including myocardial infarction, pulmonary embolism, deep vein thrombosis, arterial thrombosis, and allergic-anaphylactic reactions.

The most common adverse reactions observed in more than one subject in clinical trials (frequency >1%) were fever and headache.

6.1 Clinical Trials Experience

Because clinical trials are conducted under widely varying conditions, adverse reaction rates observed cannot be directly compared to rates in other clinical trials and may not reflect the rates observed in practice.

The safety and efficacy of fibrinogen concentrate (human) for routine prophylaxis, treatment of bleeding or surgery in subjects with congenital fibrinogen deficiency was evaluated in a retrospective, multicenter trial with a prospective one-year follow-up period. Twenty-two subjects between 2 to 78 years with a mean age of 34 years were enrolled, with treatment recorded during the retrospective period from an age of less than 1 year. Thirteen of the 22 (59.1%) subjects were female, 21 (95.5%) subjects were white, and 1 (4.5%) subject Asian [see Clinical Studies (14)].

The adverse reactions reported in the retrospective period were visual impairment, chest discomfort, chest pain, cough, wheezing, flushing, and venous thrombosis of the limb [1 event each] and dyspnea [2 events]. No adverse reactions were found in the prospective period.

6.2 Postmarketing Experience

Because postmarketing reporting of adverse reactions is voluntary and from a population of uncertain size, it is not always possible to reliably estimate the frequency of these reactions or establish a causal relationship to product exposure.

The following adverse reactions, identified by system organ class, have shown a possible causal relationship with RIASTAP.

- Allergic-anaphylactic reactions: anaphylaxis, dyspnea, rash
- Cardiovascular: thromboembolic complications such as myocardial infarction, pulmonary embolism, and deep vein thrombosis [see Warnings and Precautions (5.2)]
- General/Body as a Whole: chills, nausea, vomiting

8 USE IN SPECIFIC POPULATIONS

8.1 Pregnancy

Risk Summary

There are no studies of RIASTAP use in pregnant women. Animal reproduction studies have not been conducted with RIASTAP. It is not known whether RIASTAP can cause fetal harm when administered to a pregnant woman or can affect reproduction capacity.. In the U.S. general population, the estimated background risk of major birth defects and miscarriage in clinically recognized pregnancies is 2-4% and 15-20%, respectively.

8.2 Lactation

Risk Summary

There is no information regarding the presence of RIASTAP in human milk, its effects on the breastfed infant, or its effects on milk production. The developmental and health benefits of breastfeeding should be considered along with the mother's clinical need for RIASTAP and any potential adverse effects on the breastfed infant from RIASTAP or from the underlying maternal condition.

8.4 Pediatric Use

RIASTAP studies have included subjects below the age of 16 years. In the pharmacokinetic study [see Clinical Pharmacology (12.3)], 2 children aged 8 and 11 years and 3 adolescents aged 12, 14 and 16 years were studied. Subjects <16 years of age (n = 4) had shorter half-life (69.9 ± 8.5 h) and faster clearance (0.7 ± 0.1 mL/h/kg) compared with adults (half-life: 82.3 ± 20.0 h, clearance: 0.53 ± 0.1 mL/h/kg. The number of subjects <16 years of age in this study limits statistical interpretation.

A multicenter, non-interventional, retrospective cohort study with a prospective observational 12-month follow-up period was conducted to investigate the safety and efficacy of RIASTAP [see Clinical Studies (14)]. In this study, 11 of 22 subjects below 16 years were enrolled. Seven patients were 6 years or younger at first recorded treatment with fibrinogen concentrate (human), starting from an age of <1 year. Fibrinogen concentrate (human) was administered for prophylaxis as well as for treatment of bleeding events and for perioperative use. Ten patients younger than 18 years of age experienced bleeding events; hemostatic efficacy of fibrinogen concentrate (human) was rated as "effective" in all cases. Six patients underwent 7 surgeries and hemostatic efficacy was rated as "effective" in all cases.

8.5 Geriatric Use

The safety and efficacy of RIASTAP in the geriatric population has not been studied. There were an insufficient number of subjects in this age group to determine whether they respond differently from younger subjects.

11 DESCRIPTION

RIASTAP is a sterile, heat-treated, lyophilized fibrinogen (coagulation factor I) concentrate powder manufactured from pooled human plasma.

Fibrinogen (factor I) is a soluble plasma glycoprotein with a molecular weight of about 340 kDa. The native molecule is a dimer and consists of three pairs of polypeptide chains (Aα, Bβ and γ). Fibrinogen is a physiological substrate of three enzymes: thrombin, factor XIIIa, and plasmin.

Each RIASTAP 1 g dose vial contains 900 to 1300 mg fibrinogen, 400 to 700 mg human albumin, 375 to 660 mg L-arginine hydrochloride, 200 to 350 mg sodium chloride and 50 to 100 mg sodium citrate.

Each RIASTAP 2 g dose vial contains 1800 to 2600 mg fibrinogen, 800 to 1400 mg human albumin, 750 to 1320 mg L-arginine hydrochloride, 400 to 700 mg sodium chloride and 100 to 200 mg sodium citrate.

Sodium hydroxide and hydrochloric acid may have been used to adjust the pH. The pH of the reconstituted RIASTAP is in a range of 6.5 to 7.5.

Viral Clearance

All plasma used in the manufacture of RIASTAP is tested using serological assays for hepatitis B surface antigen and for antibodies to Human Immunodeficiency Virus (HIV)-1/2 and Hepatitis C Virus (HCV). As an additional safety measure, the plasma is tested with Nucleic Acid Testing (NAT) for Hepatitis B Virus (HBV), HCV and HIV-1 and found to be non-reactive (negative). The plasma is also screened for Hepatitis A Virus (HAV) and Human Parvovirus B19 (B19V) by NAT. Only plasma that passed virus screening is used for production, and the limit for B19V in the fractionation pool is set not to exceed 10^4 IU of B19V DNA per mL.

RIASTAP is manufactured from cryoprecipitate into a glycine precipitate, which is then further purified by multiple precipitation/adsorption steps. The manufacturing process has been demonstrated to reduce the risk of virus transmission in an additive manner: cryoprecipitation, heat treatment (+60ºC for 20 hours in an aqueous solution), two subsequent glycine precipitation steps (initial and main glycine precipitation steps), and lyophilization. These steps have been validated independently in a series of in vitro experiments for their capacity to inactivate and/or remove both enveloped and non-enveloped viruses. The results of virus clearance validation studies for RIASTAP manufacturing process are summarized in Table 1.

Table 1. Cumulative (Log10) Virus Reduction Factors for RIASTAP
Manufacturing Step | Virus Reduction Factor (log10)
Manufacturing Step | Enveloped viruses |  |  |  | Non-enveloped viruses
Manufacturing Step | HIV [HIV, human immunodeficiency virus, a model for HIV-1 and HIV-2] | BVDV [BVDV, bovine viral diarrhea virus, a model for Hepatitis C virus (HCV) and West Nile Virus (WNV)] | WNV [WNV, West Nile virus] | PRV [PRV, Pseudorabies virus, a model for large enveloped DNA viruses] | HAV [HAV, Hepatitis A virus] | CPV [CPV, canine parvovirus, a model for B19V]
Cryoprecipitation | n.d. | n.d. | n.d. | 1.6 | n.d. | 1.9
Heat Treatment | ≥5.7 | ≥9.1 | ≥8.3 | 5.4 | 5.9 | 1.4
Glycine precipitations (two subsequent steps) | 3.9 | 2.1 | n.d. | 1.8 | 1.0 | 1.6
Lyophilization | n.d. | n.d. | n.d. | n.d. | 1.7 | n.d.
Cumulative virus reduction (log10) | ≥9.6 | ≥11.2 | ≥8.3 | 8.8 | 8.6 | 4.9
Studies using human parvovirus B19, which are considered experimental in nature, have demonstrated a virus reduction factor of ≥4.5 log10 by heat treatment
n.d. not determined

12 CLINICAL PHARMACOLOGY

12.1 Mechanism of Action

During the coagulation process, thrombin cleaves the Aα and Bβ chains releasing fibrinopeptides A and B (FPA and FPB, respectively).^2 FPA is separated rapidly and the remaining molecule is a soluble fibrin monomer (fibrin I). The slower removal of FPB results in formation of fibrin II that is capable of polymerization that occurs by aggregation of fibrin monomers.^2 The resulting fibrin is stabilized in the presence of calcium ions and by activated factor XIII, which acts as a transglutaminase. Factor XIIIa-induced cross-linking of fibrin polymers renders the fibrin clot more elastic and more resistant to fibrinolysis.^3 Cross-linked fibrin is the end result of the coagulation cascade, and provides tensile strength to a primary hemostatic platelet plug and structure to the vessel wall.

12.2 Pharmacodynamic Action

Administration of RIASTAP to patients with congenital fibrinogen deficiency replaces missing or low levels of coagulation factor. Normal levels are in the range of 200 to 450 mg/dL.^4

12.3 Pharmacokinetics

A prospective, open label, uncontrolled, multicenter pharmacokinetic study was conducted in 5 females and 9 males with congenital fibrinogen deficiency (afibrinogenemia), ranging in age from 8 to 61 years (2 children, 3 adolescents, 9 adults). Each subject received a single intravenous dose of 70 mg/kg RIASTAP. Blood samples were collected to determine fibrinogen activity at baseline and up to 14 days after infusion. The pharmacokinetic parameters of RIASTAP are summarized in Table 2.

No statistically relevant difference in fibrinogen activity was observed between males and females. Subjects <16 years of age (n=4) had shorter half-life (69.9 ± 8.54 h) and faster clearance (0.73 ± 0.14 mL/h/kg) compared with subjects ≥16 years of age (half-life of 82.3 ± 20.04 h and clearance of 0.53 ± 0.07 mL/h/kg). The number of subjects <16 years of age in this study limits statistical interpretation.

The incremental in vivo recovery (IVR) was determined from levels obtained up to 4 hours post-infusion. The median incremental IVR was 1.7 mg/dL (range 1.30 – 2.73 mg/dL) increase per mg/kg. The median in vivo recovery indicates that a dose of 70 mg/kg will increase fibrinogen plasma concentration in patients by approximately 120 mg/dL.

The pharmacokinetic analysis using fibrinogen antigen data (ELISA) was concordant with the fibrinogen activity (Clauss assay).

Table 2. Pharmacokinetic Parameters (n=14) for Fibrinogen Activity
Parameters | Mean ± SD (range)
Half-life [h] | 78.7 ± 18.13 (55.73-117.26)
Cmax [mg/dL] | 140 ± 27 (100-210)
AUC for dose of 70 mg/kg [mg*h/mL] | 124.3 ± 24.16 (81.73-156.40)
Clearance [mL/h/kg] | 0.59 ± 0.13 (0.45-0.86)
Mean residence time [h] | 92.8 ± 20.11 (66.14-126.44)
Volume of distribution at steady state [mL/kg] | 52.7 ± 7.48 (36.22-67.67)

h: hours

14 CLINICAL STUDIES

The efficacy of RIASTAP is based on maximum clot firmness, a measure of clot structural integrity that reflects the underlying effectiveness of the fibrinogen present to form a fibrin clot. A pharmacokinetic study evaluated single-dose PK [see Clinical Pharmacology (12.3)] and maximum clot firmness (MCF) in subjects with afibrinogenemia. MCF was determined by thromboelastometry (ROTEM) testing and was used to demonstrate functional activity of replacement fibrinogen when a fixed dose of RIASTAP was administered. Clot firmness is a functional parameter that depends on activation of coagulation, fibrinogen content of the sample and polymerization/crosslinking of the fibrin network. Thromboelastometry has been shown to be a functional marker for assessment of fibrinogen content and for effects of fibrinogen supplementation on clinical efficacy.^5

For each subject, MCF was determined before (baseline) and one hour after single dose administration of RIASTAP. RIASTAP was found to be effective in increasing clot firmness in subjects with congenital fibrinogen deficiency (afibrinogenemia) as measured by thromboelastometry. The study results demonstrated that MCF values were significantly higher after administration of RIASTAP than at baseline (see Table 3). Mean change from pre-infusion to 1 hour post-infusion was 8.9 mm in the primary analysis (9.9 mm for subjects <16years old and 8.5 mm for subjects ≥16 to <65 years old). Mean change in MCF values closely approximated levels expected from adding known amounts of fibrinogen to plasma in vitro.^6

Table 3. MCF [mm] (ITT population)
Time point | n | Mean ± SD | Median (range)
Pre-infusion | 13 | 0 ± 0 | 0 (0-0)
1 hour post-infusion | 13 | 10.3 ± 2.7 | 10.0 (6.5-16.5)
Mean change (primary analysis) [p-value was <0.0001.] | 15 [The mean change was set to 0 for 2 subjects with missing MCF data.] | 8.9 ± 4.4 | 9.5 (0-16.5)
MCF = maximum clot firmness; mm = millimeter; ITT = intention-to-treat.

A multicenter, non-interventional, retrospective cohort study with a prospective observational 12-month follow-up period was conducted to investigate the safety and efficacy of RIASTAP for the treatment of acute bleeding events, routine prophylaxis, and perioperative hemostasis in subjects with congenital fibrinogen deficiency.

A total of 22 subjects were enrolled. Eleven of the 22 subjects enrolled were 16 years of age or younger and 11 subjects were 18 years of age or older at the time of first recorded treatment, which was documented in the retrospective period prior to enrollment.

In the retrospective period, the hemostatic efficacy was rated by the investigator as "effective" for 97% of the acute bleeding events and for 97.5% of the bleeding events during surgery, and prophylactic use of RIASTAP was associated to a low median ABR of 1.43 bleeding events per year. The efficacy during the prospective period was consistent with that observed for the retrospective period: hemostatic efficacy was rated by the investigator as "effective" for 100% of bleeding events and during surgery, and the median ABR was also low at 1.26 bleeding events per year during routine prophylaxis with RIASTAP.

15 REFERENCES

1. Peyvandi F, Haertal S, Knaub S, et al. Incidence of bleeding symptoms in 100 patients with inherited afibrinogenemia or hypofibrinogenemia. J Thromb Haemost 2006; 4:1634-7.
2. Kreuz W, Meili E, Peter-Salonen K, et al. Pharmacokinetic properties of a pasteurized fibrinogen concentrate. Transfusion and Apheresis Science 2005; 32:239-46.
3. Colman R, Clowes A, George J, et al. Overview of Hemostasis. In: Hemostasis and Thrombosis: Basic Principles and Clinical Practice (5th ed.). Colman R, Clowes A, George J, Goldhaber S, Marder VJ (eds.). Lippincott Williams & Wilkins, Philadelphia 2006:11-14.
4. Kreuz W, Meili E, Peter-Salonen K, et al. Efficacy and tolerability of a pasteurized human fibrinogen concentrate in patients with congenital fibrinogen deficiency. Transfusion and Apheresis Science 2005; 32:247-253.
5. Fries D, Innerhofer P, Reif C, et al. The Effect of Fibrinogen Substitution on Reversal of Dilutional Coagulopathy: An In Vitro Model. Anesth Analg 2006; 102:347-351.
6. Kalina U, Stöhr HA, Bickhard H, et. al. Rotational thromboelastography for monitoring of fibrinogen concentrate therapy in fibrinogen deficiency. Blood Coagulation and Fibrinolysis. 2008; 19:777-783.

16 HOW SUPPLIED/STORAGE AND HANDLING

- RIASTAP is supplied in a single-dose vial.
- Each carton contains one vial of RIASTAP.
- Components are not made with natural rubber latex.
- RIASTAP contains no preservative.
- The actual potency of fibrinogen concentrate in milligram (mg) is stated on each RIASTAP vial label and carton.

The product presentation includes a package insert and the following component:

Table 4. How Supplied
Presentation | Carton NDC Number | Component | Color coding
1 g dose vial | 63833-891-51 | RIASTAP in a single-dose vial (NDC 63833-891-90) | red
2 g dose vial | 63833-892-51 | RIASTAP in a single-dose vial (NDC 63833-892-90) | green

STORAGE AND HANDLING

- When stored at temperatures of 2-8°C (36-46°F), RIASTAP is stable for the period indicated by the expiration date on the carton and vial label (up to 60 months). Do not use RIASTAP beyond the expiration date.
- Keep RIASTAP in its original carton until ready to use.
- Do not freeze. Protect from light.
- Discard partially used vials.

17 PATIENT COUNSELING INFORMATION

- Allergic Reactions
  Inform patients of the early signs of allergic or hypersensitivity reactions to RIASTAP, including hives, chest tightness, wheezing, hypotension, and anaphylaxis. Advise them to notify their physician immediately if they experience any of these symptoms [see Warnings and Precautions (5.1)].

- Thrombosis
  Inform patients that thrombosis with or without embolization has been reported with the use of RIASTAP. Any symptoms of thrombotic events such as unexplained pleuritic, chest and/or leg pain or edema, hemoptysis, dyspnea, tachypnea or unexplained neurologic symptoms should be reported to their physician immediately [see Warnings and Precautions (5.2)].

- Transmissible Infectious Agents
  Inform patients that RIASTAP is made from human plasma (part of the blood) and may carry a risk of transmitting infectious agents e.g., viruses, the variant Creutzfeldt-Jakob disease (vCJD) agent and, theoretically, the Creutzfeldt-Jakob disease (CJD) agent. Explain that the risk of transmitting an infection agent using RIASTAP has been reduced by screening plasma donors, testing the donated plasma for certain virus infections, and incorporating a process demonstrated to inactivate and/or remove certain viruses during manufacturing. Symptoms of possible virus infection include headache, fever, nausea, vomiting, weakness, malaise, diarrhea, or, in the case of hepatitis, jaundice [see Warnings and Precautions (5.3)].

Manufactured by:
CSL Behring GmbH
35041 Marburg Germany
US License No. 1765

Distributed by:
CSL Behring LLC
Kankakee, IL 60901 USA

PRINCIPAL DISPLAY PANEL - 50 mL Vial Label

NDC 63833-891-90

Fibrinogen Concentrate
(Human)
RiaSTAP®

For Intravenous
Administration Only

Manufactured by:
CSL Behring GmbH
35041 Marburg, Germany
US License No. 1765

Distributed by:
CSL Behring LLC
Kankakee, IL 60901 USA

PRINCIPAL DISPLAY PANEL - 50 mL Vial Carton

NDC 63833-891-51
One single-dose Vial

1g Range

Fibrinogen Concentrate (Human)

RiaSTAP®

One single-dose vial containing
approximately 1 g of lyophilized
fibrinogen for reconstitution.

For Intravenous Administration Only

CSL Behring

PRINCIPAL DISPLAY PANEL - 100 mL Vial Label

NDC 63833-892-90

Fibrinogen Concentrate (Human)

RiaSTAP®

For Intravenous Administration Only

When reconstituted, each vial contains
1800–2600 mg of Fibrinogen,
800–1400 mg of Human albumin,
750–1320 mg of L-arginine hydrochloride,
400–700 mg of Sodium chloride and
100–200 mg of Sodium citrate.
Contains no preservative.

When stored at temperatures of 2–8°C (36–46°F),
RiaSTAP® is stable for the period indicated by the
expiration date on the carton and vial label
(up to 60 months).

Manufactured by:
CSL Behring GmbH
35041 Marburg,
Germany
US License No. 1765

Distributed by:
CSL Behring LLC
Kankakee, IL 60901
USA

PRINCIPAL DISPLAY PANEL - 100 mL Vial Carton

NDC 63833-892-51
One single-dose Vial

2g Range

Fibrinogen Concentrate
(Human)

RiaSTAP®

One single-dose vial containing approximately
2 g of lyophilized fibrinogen for reconstitution.

For Intravenous Administration Only

CSL Behring